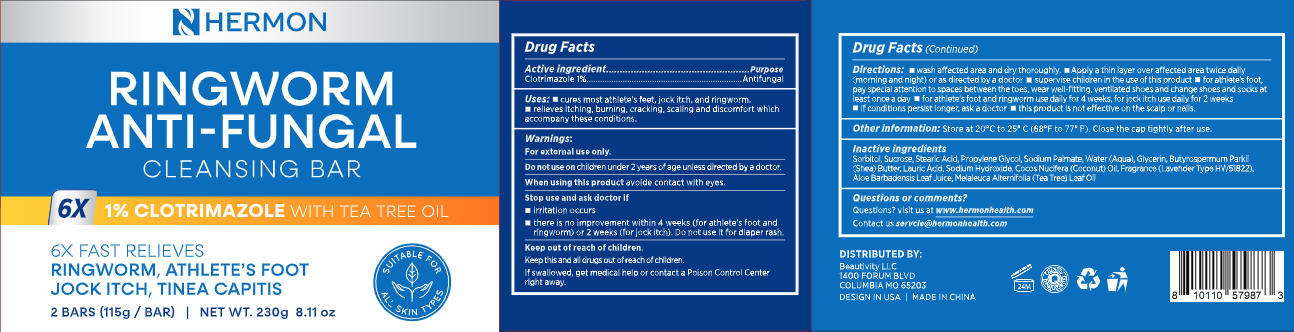 DRUG LABEL: Hermon Ringworm Antifungal soap.
NDC: 85398-026 | Form: SOAP
Manufacturer: Beautivity LLC
Category: otc | Type: HUMAN OTC DRUG LABEL
Date: 20260213

ACTIVE INGREDIENTS: CLOTRIMAZOLE 2.3 g/230 g
INACTIVE INGREDIENTS: WATER; PROPYLENE GLYCOL; FRAGRANCE LAVENDER ROSE ORC1004596; SODIUM HYDROXIDE; ALOE BARBADENSIS LEAF JUICE; BUTYROSPERMUM PARKII (SHEA) BUTTER; SUCROSE; STEARIC ACID; COCOS NUCIFERA (COCONUT) OIL; MELALEUCA ALTERNIFOLIA (TEA TREE) LEAF OIL; SODIUM PALMATE; SORBITOL; GLYCERIN; LAURIC ACID

Initial Drug Listing - Hermon Ringworm Antifungal Soap-Pack2

ACTIVE INGREDIENT

Clotrimazole 1%

PURPOSE

Antifungal

DOSAGE AND ADMINISTRATION

- cures most athlete's feet,jock itch,and ringworm.
- relieves itching,burning,cracking, scaling and discomfort which accompany these conditions.

WARNINGS

For external use only.

DO NOT USE

children under 2 years ofage unless directed by a doctor.

WHEN USING

avoide contact with eyes.

ASK DOCTOR/PHARMACIST

- Irritation occurs
- there is no improvement within 4 weeks (for athlete's foot and ringworm) or 2 weeks (for jock itch). Do not use it for diaper rash.

KEEP OUT OF REACH OF CHILDREN

Keep this and all drugs out of reach of children.
If swallowed, get medical help or contact a Poison Control Center right away.

INDICATIONS AND USAGE

- Wash affected area and dry thoroughly.
- Apply a thin layer over affected area twice daily(morning and night) or as directed by a doctor
- Supervise children in the use of this product
- For athlete's foot, pay special attention to spaces between the toes, wear well-fitting,ventilated shoes and change shoes and socks atleast once a day
- For athlete's foot and ringworm use daily for 4 weeks,for jock itch use daily for 2 weeks
- If conditions persist longer,ask a doctor
- This product is not effective on the scalp or nails.

OTHER SAFETY INFORMATION

Store at 20eC to 252 C (68eF to 77e F). Close the cap tightly after use.

INACTIVE INGREDIENT

Sorbitol, Sucrose, Stearic Acid, Propylene Glvcol, Sodium Palmate, Water (Aqua),Glycerin,Butyrospermum Parkil(Shea) Butter, Lauric Acid, Sodium Hydroxide, Cocos Nucifera (Coconut) Oil, Fragrance (Lavender Type HW51822), Aloe Barbadensis Leaf Juice, Melaleuca Alternifolia (Tea Tree) Leaf Oil

Questions? visit us at www.hermonhealth.com

Contact us servcie@hermonhealth.com